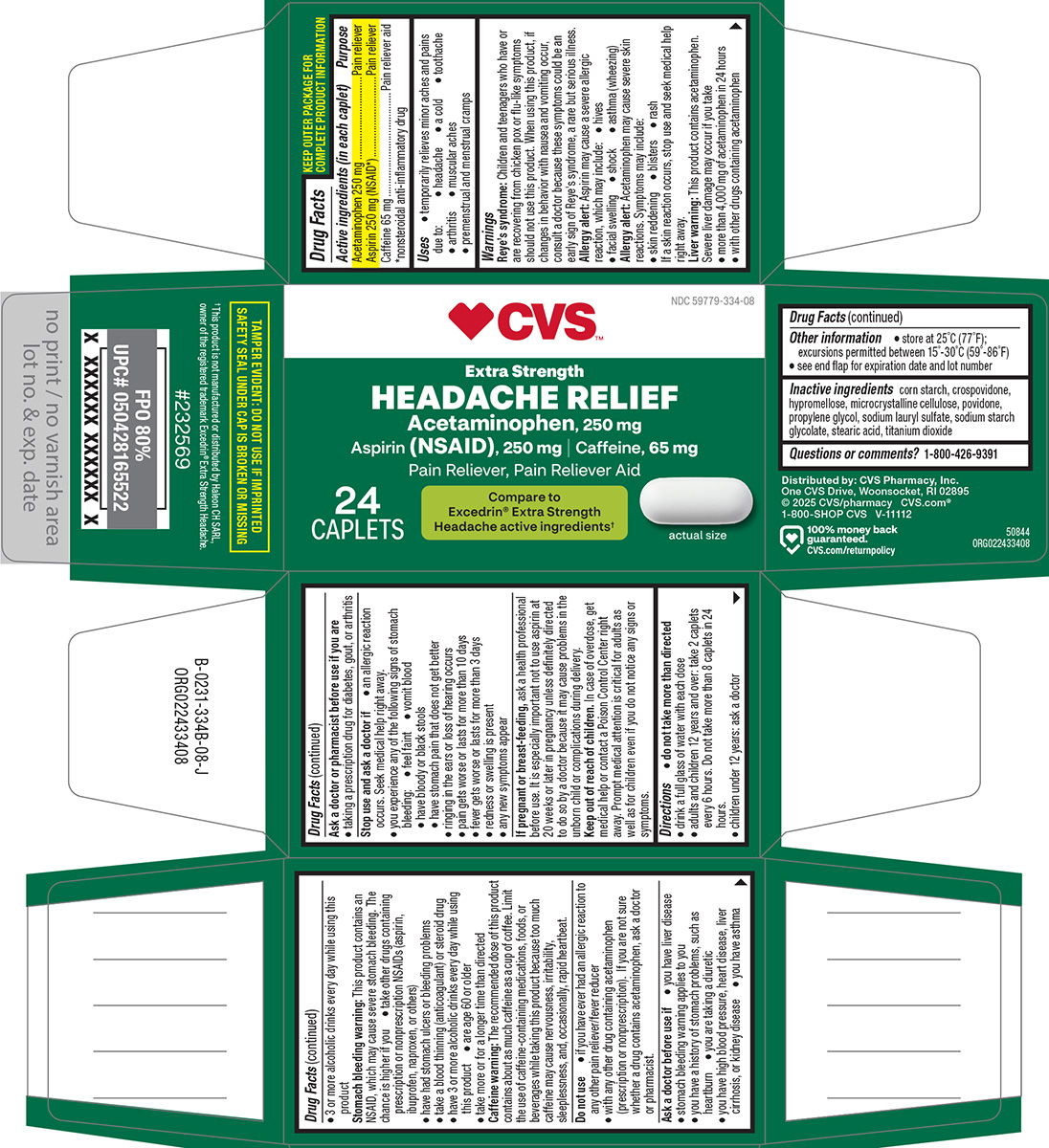 DRUG LABEL: Headache Relief
NDC: 59779-334 | Form: TABLET, FILM COATED
Manufacturer: CVS Pharmacy
Category: otc | Type: HUMAN OTC DRUG LABEL
Date: 20260105

ACTIVE INGREDIENTS: ACETAMINOPHEN 250 mg/1 1; ASPIRIN 250 mg/1 1; CAFFEINE 65 mg/1 1
INACTIVE INGREDIENTS: STARCH, CORN; CROSPOVIDONE, UNSPECIFIED; HYPROMELLOSE, UNSPECIFIED; MICROCRYSTALLINE CELLULOSE; POVIDONE, UNSPECIFIED; PROPYLENE GLYCOL; SODIUM LAURYL SULFATE; SODIUM STARCH GLYCOLATE TYPE A POTATO; STEARIC ACID; TITANIUM DIOXIDE

CVS 44-334B-H

Active ingredients (in each caplet)

Acetaminophen 250 mg
Aspirin 250 mg (NSAID*)
Caffeine 65 mg
*nonsteroidal anti-inflammatory drug

Purpose

Pain reliever
Pain reliever
Pain reliever aid

Uses

- temporarily relieves minor aches and pains due to:
  - toothache
  - arthritis
  - a cold
  - headache
  - muscular aches
  - premenstrual and menstrual cramps

Warnings

Reye’s syndrome: Children and teenagers who have or are recovering from chicken pox or flu-like symptoms should not use this product. When using this product, if changes in behavior with nausea and vomiting occur, consult a doctor because these symptoms could be an early sign of Reye's syndrome, a rare but serious illness.

Allergy alert: Aspirin may cause a severe allergic reaction, which may include:

- shock
- facial swelling
- hives
- asthma (wheezing)

Allergy alert: Acetaminophen may cause severe skin reactions. Symptoms may include:

- skin reddening
- blisters
- rash

If a skin reaction occurs, stop use and seek medical help right away.

Liver warning: This product contains acetaminophen. Severe liver damage may occur if you take

- more than 4,000 mg of acetaminophen in 24 hours
- 3 or more alcoholic drinks every day while using this product
- with other drugs containing acetaminophen

Stomach bleeding warning: This product contains an NSAID, which may cause severe stomach bleeding. The chance is higher if you

- are age 60 or older
- have had stomach ulcers or bleeding problems
- take a blood thinning (anticoagulant) or steroid drug
- take other drugs containing prescription or nonprescription NSAIDs (aspirin, ibuprofen, naproxen, or others)
- have 3 or more alcoholic drinks every day while using this product
- take more or for a longer time than directed

Caffeine warning: The recommended dose of this product contains about as much caffeine as a cup of coffee. Limit the use of caffeine-containing medications, foods, or beverages while taking this product because too much caffeine may cause nervousness, irritability, sleeplessness, and, occasionally, rapid heartbeat.

Do not use

- if you have ever had an allergic reaction to any other pain reliever/fever reducer
- with any other drug containing acetaminophen (prescription or nonprescription). If you are not sure whether a drug contains acetaminophen, ask a doctor or pharmacist.

Ask a doctor before use if

- you have liver disease
- you have asthma
- stomach bleeding warning applies to you
- you have a history of stomach problems, such as heartburn
- you are taking a diuretic
- you have high blood pressure, heart disease, liver cirrhosis, or kidney disease

Ask a doctor or pharmacist before use if you are

- taking a prescription drug for diabetes, gout, or arthritis

Stop use and ask a doctor if

- an allergic reaction occurs. Seek medical help right away.
- you experience any of the following signs of stomach bleeding:
  - feel faint
  - vomit blood
  - have bloody or black stools
  - have stomach pain that does not get better
- ringing in the ears or loss of hearing occurs
- pain gets worse or lasts for more than 10 days
- fever gets worse or lasts for more than 3 days
- redness or swelling is present
- any new symptoms appear

If pregnant or breast-feeding,

ask a health professional before use. It is especially important not to use aspirin at 20 weeks or later in pregnancy unless definitely directed to do so by a doctor because it may cause problems in the unborn child or complications during delivery.

Keep out of reach of children.

In case of overdose, get medical help or contact a Poison Control Center right away. Prompt medical attention is critical for adults as well as for children even if you do not notice any signs or symptoms.

Directions

- do not take more than directed
- drink a full glass of water with each dose
- adults and children 12 years and over: take 2 caplets every 6 hours. Do not take more than 8 caplets in 24 hours.
- children under 12 years: ask a doctor

Other information

- store at 25°C (77°F); excursions permitted between 15°-30°C (59°-86°F)
- see end flap for expiration date and lot number

Inactive ingredients

corn starch, crospovidone, hypromellose, microcrystalline cellulose, povidone, propylene glycol, sodium lauryl sulfate, sodium starch glycolate, stearic acid, titanium dioxide

Questions or comments?

1-800-426-9391

Principal Display Panel

♥︎CVS™

NDC 59779-334-08

Extra Strength
HEADACHE RELIEF
Acetaminophen, 250 mg
Aspirin (NSAID), 250 mg | Caffeine, 65 mg
Pain Reliever, Pain Reliever Aid

Compare to Excedrin® Extra Strength Headache
active ingredients†

24 CAPLETS

Actual Size

TAMPER EVIDENT: DO NOT USE IF IMPRINTED
SAFETY SEAL UNDER CAP IS BROKEN OR MISSING

Distributed by: CVS Pharmacy, Inc.
One CVS Drive, Woonsocket, RI 02895
© 2025 CVS/pharmacy CVS.com® 1-800-SHOP CVS
V-11112

† This product is not manufactured or distributed by Haleon CH SARL,
owner of the registered trademark Excedrin® Extra Strength Headache.
50844 ORG022433408

CVS 44-334